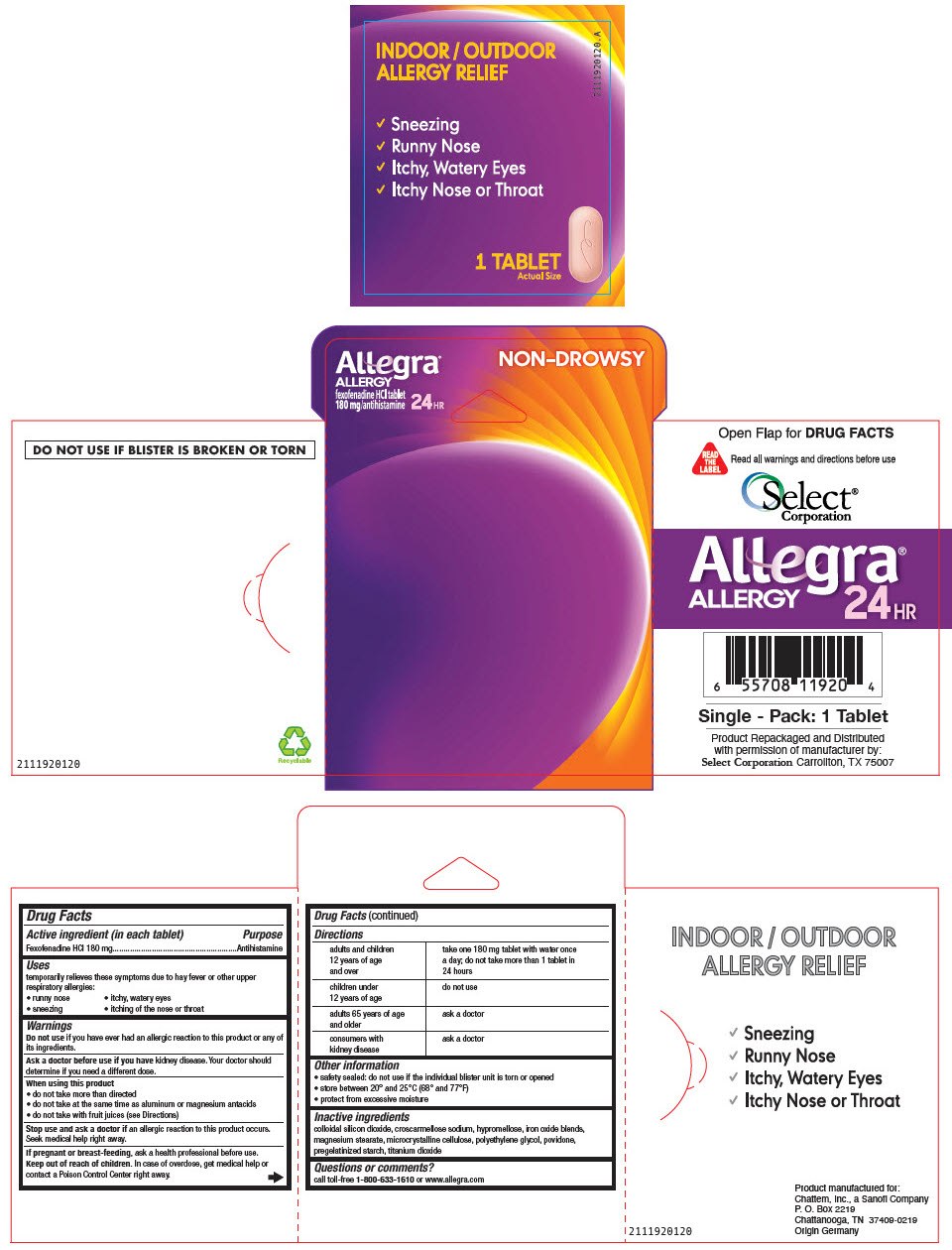 DRUG LABEL: Allegra Allergy
NDC: 52904-190 | Form: TABLET, FILM COATED
Manufacturer: Select Corporation
Category: otc | Type: HUMAN OTC DRUG LABEL
Date: 20220414

ACTIVE INGREDIENTS: Fexofenadine hydrochloride 60 mg/1 1
INACTIVE INGREDIENTS: silicon dioxide; croscarmellose sodium; HYPROMELLOSE, UNSPECIFIED; magnesium stearate; MICROCRYSTALLINE CELLULOSE; polyethylene glycol, unspecified; POVIDONE, UNSPECIFIED; titanium dioxide; STARCH, CORN; brown iron oxide

Allegra® Allergy

Drug Facts

Active ingredient (in each tablet)

Fexofenadine HCl 180 mg

Purpose

Antihistamine

Uses

temporarily relieves these symptoms due to hay fever or other upper respiratory allergies:

- runny nose
- itchy, watery eyes
- sneezing
- itching of the nose or throat

Warnings

Do not use if you have ever had an allergic reaction to this product or any of its ingredients.

Ask a doctor before use if you have kidney disease. Your doctor should determine if you need a different dose.

When using this product

- do not take more than directed
- do not take at the same time as aluminum or magnesium antacids
- do not take with fruit juices (see Directions)

Stop use and ask a doctor if an allergic reaction to this product occurs. Seek medical help right away.

PREGNANCY OR BREAST FEEDING

If pregnant or breast-feeding, ask a health professional before use.

Keep out of reach of children. In case of overdose, get medical help or contact a Poison Control Center right away.

Directions

adults and children 12 years of age and over | take one 180 mg tablet with water once a day; do not take more than 1 tablet in 24 hours
children under 12 years of age | do not use
adults 65 years of age and older | ask a doctor
consumers with kidney disease | ask a doctor

Other information

- safety sealed: do not use if the individual blister unit is torn or opened
- store between 20° and 25°C (68° and 77°F)
- protect from excessive moisture

Inactive ingredients

colloidal silicon dioxide, croscarmellose sodium, hypromellose, iron oxide blends, magnesium stearate, microcrystalline cellulose, polyethylene glycol, povidone, pregelatinized starch, titanium dioxide

Questions or comments?

call toll-free 1-800-633-1610 or www.allegra.com

Product Repackaged and Distributed
with permission of manufacturer by:
Select Corporation Carrollton, TX 75007

PRINCIPAL DISPLAY PANEL - 1 Tablet Pouch Blister Pack

Allegra®
ALLERGY
fexofenadine HCl tablet
180 mg/antihistamine
24HR

NON-DROWSY

INDOOR / OUTDOOR
ALLERGY RELIEF

2111920120.A

✓ Sneezing
✓ Runny Nose
✓ Itchy, Watery Eyes
✓ Itchy Nose or Throat

1 TABLET
Actual Size